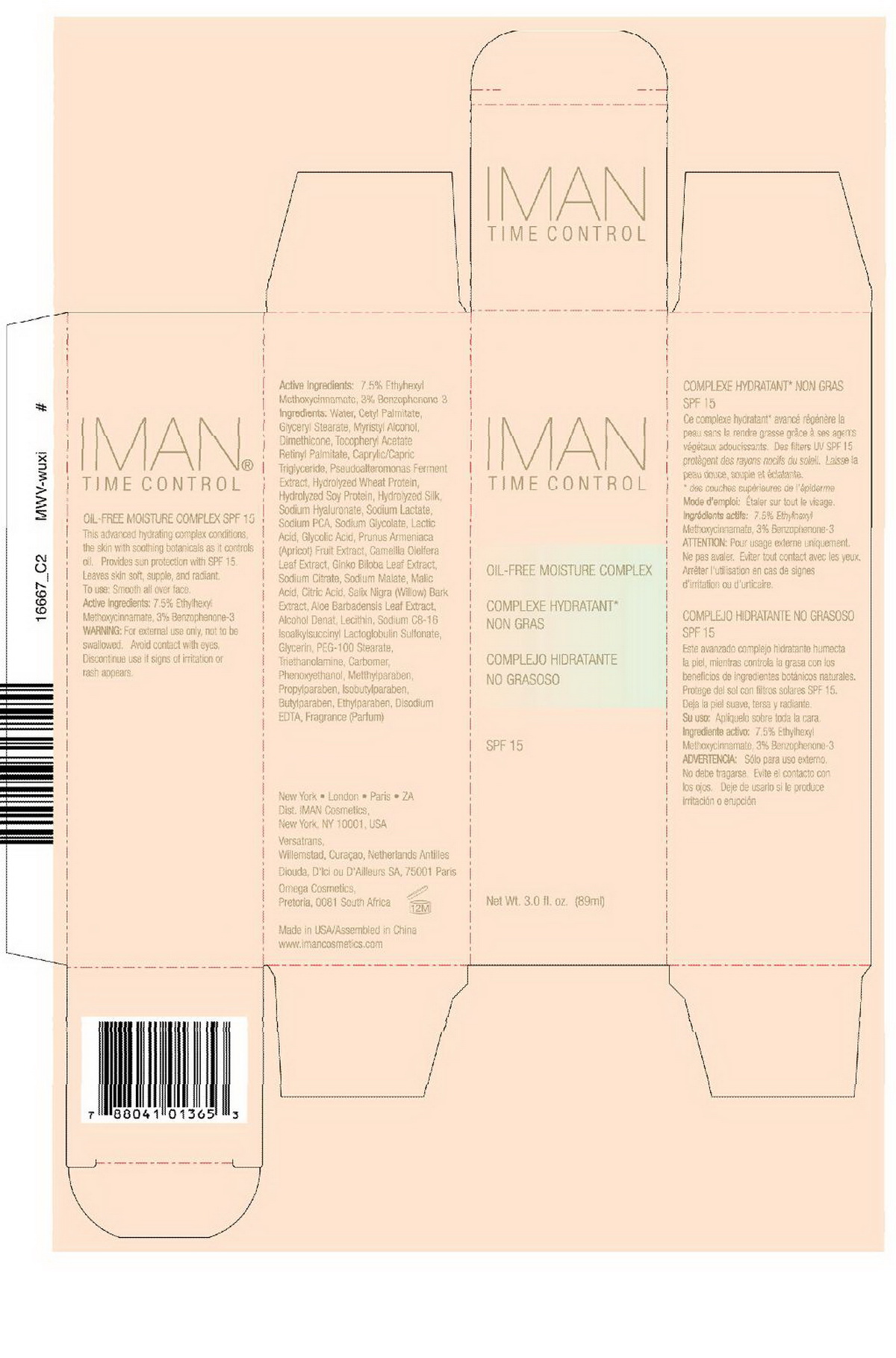 DRUG LABEL: Iman Time Control Oil Free Moisture Complex SPF 15
NDC: 50950-002 | Form: CREAM
Manufacturer: Sheencolor Biotech Co., Ltd.
Category: otc | Type: HUMAN OTC DRUG LABEL
Date: 20100905

ACTIVE INGREDIENTS: OCTINOXATE 7.5 g/100 g; OXYBENZONE 3 g/100 g
INACTIVE INGREDIENTS: WATER 75.5795 g/100 g; ANHYDROUS TRISODIUM CITRATE 0.0066 g/100 g; GLYCERIN 0.71 g/100 g; GLYCERYL MONOSTEARATE 2.5 g/100 g; CETYL PALMITATE 2.50 g/100 g; WILLOW BARK 0.08 g/100 g; TEA LEAF OIL 0.02 g/100 g; POLYOXYL 100 STEARATE 0.8 g/100 g; ALPHA-TOCOPHEROL ACETATE 0.1 g/100 g; APRICOT JUICE 0.02 g/100 g; HYALURONATE SODIUM 0.10 g/100 g; GINKGO 0.02 g/100 g; ANHYDROUS CITRIC ACID 0.0003 g/100 g; ALOE VERA LEAF 0.5 g/100 g; MYRISTYL ALCOHOL 2.0 g/100 g; ALCOHOL 0.1 g/100 g; TROLAMINE 0.512 g/100 g; CARBOMER HOMOPOLYMER TYPE A 0.5 g/100 g; PHENOXYETHANOL 0.798 g/100 g; METHYLPARABEN 0.17 g/100 g; PROPYLPARABEN 0.022 g/100 g; ISOBUTYLPARABEN 0.022 g/100 g; BUTYLPARABEN 0.044 g/100 g; ETHYLPARABEN 0.044 g/100 g; EDETATE DISODIUM 0.1 g/100 g; LECITHIN, SOYBEAN 0.1 g/100 g; DIMETHICONE 1.5 g/100 g; VITAMIN A PALMITATE 0.1 g/100 g; MALIC ACID 0.0003 g/100 g; GLYCOLIC ACID 0.0003 g/100 g; LACTIC ACID 0.0027 g/100 g; SODIUM LACTATE 0.02 g/100 g; SODIUM GLYCOLATE 0.0066 g/100 g; SODIUM PYRROLIDONE CARBOXYLATE 0.0066 g/100 g; MEDIUM-CHAIN TRIGLYCERIDES 0.1 g/100 g

Drug Fact

Active Ingredients:

7.5% Ethylhexyl Methoxycinnamate, 3.0% Benzophenone-3

PURPOSE

This advanced hydrating complex conditions the skin with soothing botanics as it controls oil. Provides sun protection with SPF 15, leaves skin soft, supple, and radiant.

DOSAGE AND ADMINISTRATION

To Use: Smooth all over face

Warnings:

For external use only, not to be swallowed. Avoid contact with eyes. Discontinue use if signs of irritation or rash appear.

Inactive Ingredients

Water, Cetyl Palmitate, Glyceryl Stearate, Myristate Alcohol, Dimethicone, Tocopheryl Acetate (Vitamin E), Retinyl Palmitate, Caprylic/Capric Triglyceride, Pseudoalteromonas Ferment Extract, Hydrolyzed Wheat Protein, Hydrolyzed Soy Protein, Hydrolyzed Silk, Sodium Hyaluronate, Sodium Lactate, Sodium PCA, Sodium Glycotate, Lactic Acid, Glycolic Acid, Malic Acid, Citric Acid, Sodium Citrate, Sodium Malate, Prunus Armeniaca Fruit Extract, Ginkgo Biloba Leaf Extract, Salix Nigra (Willow) Bark Extract, Sodium C8-16 Isoalkylsuccinyl Lactoglobulin Sulfonate, Aloe Barbadensis Leaf Extract, Alcohol Denat, Lecithin, Glycerin, PEG-100 Stearate, Triethanolamine, Phenoxyethanol, Carbomer, Methylparaben, Propylparaben, Isobutylparaben, Butylparaben, Ethylparaben, Disodium EDTA, Fragrance (Parfum)

PACKAGE LABEL

labe